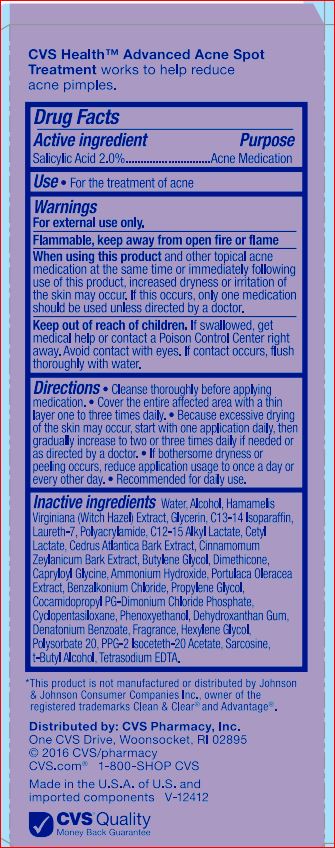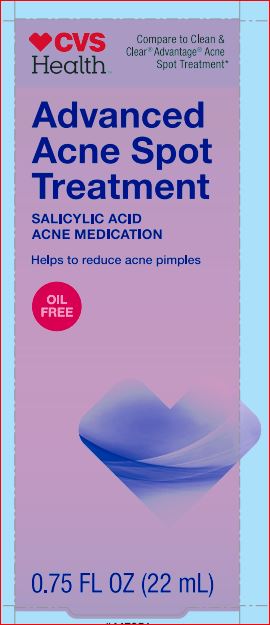 DRUG LABEL: Advanced Acne Spot Treatment
NDC: 59779-343 | Form: LOTION
Manufacturer: CVS
Category: otc | Type: HUMAN OTC DRUG LABEL
Date: 20171226

ACTIVE INGREDIENTS: Salicylic Acid 2 g/100 mL
INACTIVE INGREDIENTS: Water; Alcohol; HAMAMELIS VIRGINIANA TOP WATER; Glycerin; C13-14 Isoparaffin; Laureth-7; C12-15 Alkyl Lactate; Cetyl Lactate; CEDRUS ATLANTICA BARK; CINNAMON BARK OIL; Butylene Glycol; Capryloyl Glycine; AMMONIA; PURSLANE; Benzalkonium Chloride; Propylene Glycol; CYCLOMETHICONE 5; Phenoxyethanol; Dehydroxanthan Gum; Denatonium Benzoate; Polysorbate 20; PPG-2 Isoceteth-20 Acetate; Sarcosine; TERT-BUTYL ALCOHOL; EDETATE SODIUM; COCAMIDOPROPYL PROPYLENE GLYCOL-DIMONIUM CHLORIDE PHOSPHATE

Active ingredient Purpose

Salicylic Acid – 2.00% Acne Medication

Use

For treatment of acne

Warnings For external use only

Flammable. Keep away from fire or flame.

When using this product and other topical acne medications at the same time or immediately following use of this product, increased dryness or irritation of the skin may occur. If this occurs, only one medication should be used unless directed by a doctor.

Keep out of reach of the children
If product is swallowed, get medical help or contact a Poison Control Center right away. Avoid contact with eyes. If contact occurs, flush thoroughly with water

DOSAGE AND ADMINISTRATION

Directions • cleans the skin thoroughly before applying medication • cover the entire affected area with a thin layer one to three times a day • If bothersome dryness or peeling occurs, reduce application to once a day or every other day. • Recomended for daily use.

INACTIVE INGREDIENT

Inactive ingredients :Water, Alcohol, Hamamelis Virginiana (Witch Hazel) Extract, Glycerin, C13-14 Isoparaffin, Laureth-7, Polyacrylamide
C12-15 Alkyl Lactate, Cetyl Lactate, Cedrus Atlantica Bark Extract, Cinnamomum Zeylanicum Bark Extract, Butylene Glycol, Dimethicone, Capryloyl Glycine, Ammonium Hydroxide, Portulaca Oleracea Extract, Benzalkonium Chloride, Propylene Glycol, Cocamidopropyl PG-Dimonium , hloride Phosphate, Cyclopentasiloxane, Phenoxyethanol, Dehydroxanthan Gum, Denatonium Benzoate, Fragrance, Hexylene Glycol, Polysorbate 20, PPG-2 Isoceteth-20 Acetate, Sarcosine, t-Butyl Alcohol, Tetrasodium EDTA